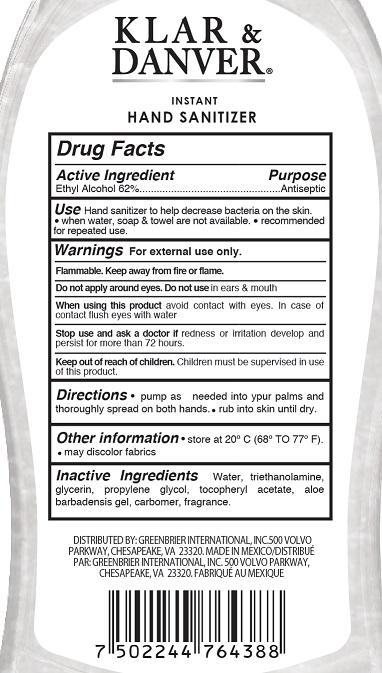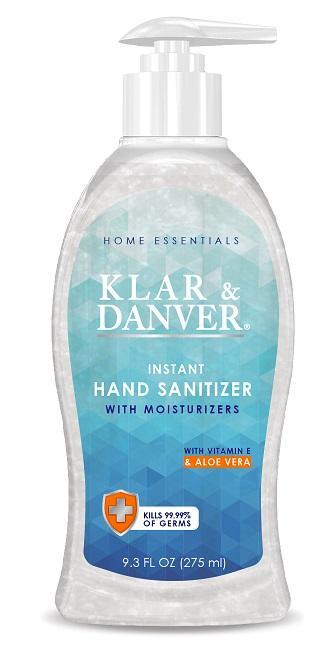 DRUG LABEL: KLAR and DANVER INSTANT HAND SANTIZER
NDC: 33992-8010 | Form: GEL
Manufacturer: Greenbrier International, Inc.
Category: otc | Type: HUMAN OTC DRUG LABEL
Date: 20191212

ACTIVE INGREDIENTS: ALCOHOL 620 mg/1 mL
INACTIVE INGREDIENTS: WATER; TROLAMINE; GLYCERIN; PROPYLENE GLYCOL; TOCOPHEROL; ALOE

KLAR & DANVER HAND SANITIZER

DRUG FACTS

ACTIVE INGREDIENT

Ethyl Alcohol 62%

Purpose

Antiseptic

Use

Hand sanitizer to help decrease bacteria on the skin.

When water, soap and towel are not available

Recommended for repeated use

Warnings

For external use only.

Flammable. Keep away from fire and flame

Do not apply around eyes. Do not use in ears and mouth

When using this product

avoid contat with eyes. In case of contact flush with water.

Sop use andask a doctor if

redness or irritation develop and persist formore than 72 hours.

Keep out of reach of children

Children must be supervised in use of this product

Directions

pump as needed ito your palms and thoroughly spread on both hands

rub into skin until dry.

Other Informatio

Store at 20C (68 to 77F)

may discolor fabrics

Inactive Ingredients

Water, triethanolamine, glycerin, propylene glycol, tocopheryl acetate, aloe barbadensis gel, carbomer, fragrance.

DISTRIBUTED BY GREENBRIER INTERNATIONAL INC

500 VOLVO PARKWAY, CHESAPEAKE, VA 23320. MADE IN MEXICO